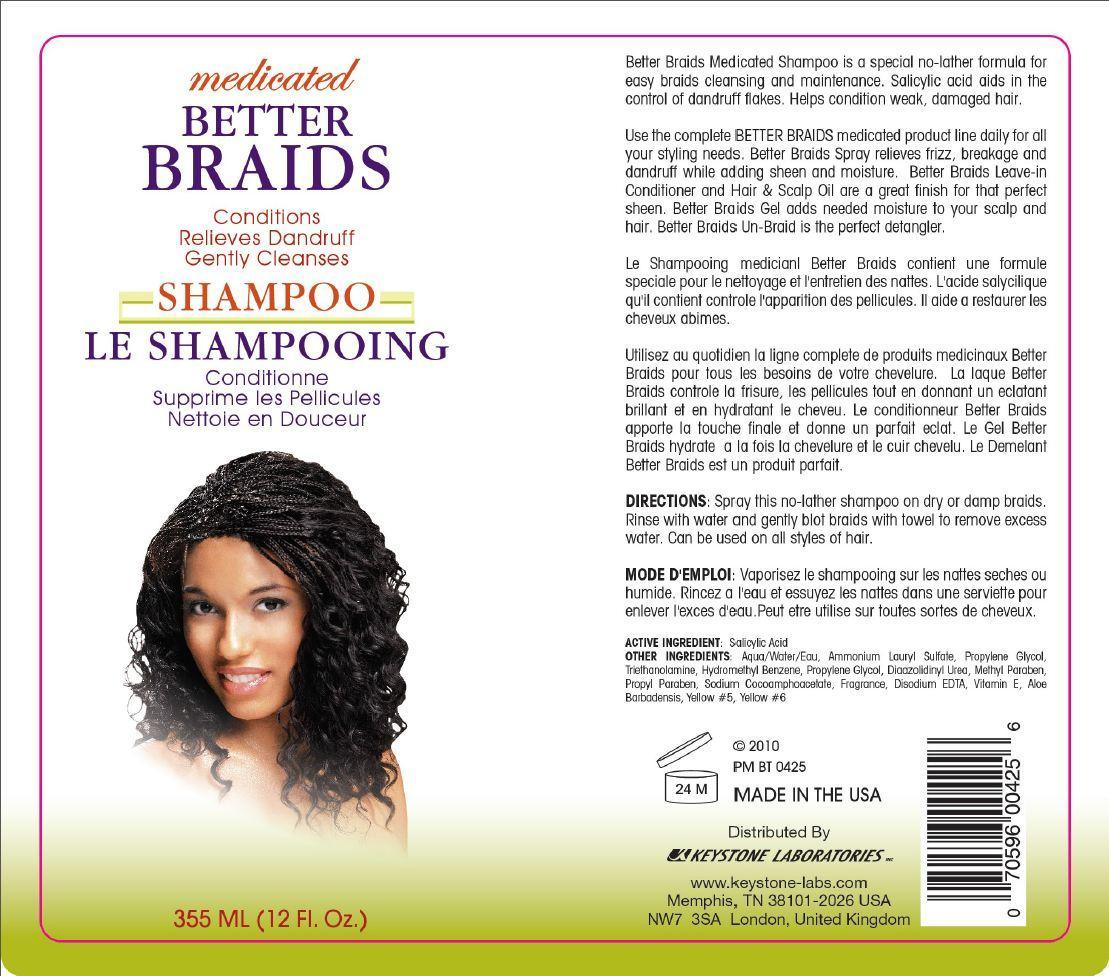 DRUG LABEL: Better Braids
NDC: 58318-001 | Form: SHAMPOO
Manufacturer: Keystone Laboratories
Category: otc | Type: HUMAN OTC DRUG LABEL
Date: 20130926

ACTIVE INGREDIENTS: SALICYLIC ACID 0.24 mg/355 mL
INACTIVE INGREDIENTS: WATER; AMMONIUM LAURYL SULFATE; PROPYLENE GLYCOL; TROLAMINE; BENZYL ALCOHOL; DIAZOLIDINYL UREA; OLEALKONIUM CHLORIDE; EDETATE DISODIUM; .ALPHA.-TOCOPHEROL; ALOE VERA LEAF; FD&C YELLOW NO. 5; FD&C YELLOW NO. 6; METHYLPARABEN; PROPYLPARABEN; SODIUM COCOAMPHOACETATE

Active Ingredient: Salicylic Acid

PURPOSE

medicated BETTER BRAIDS SHAMPOO

Conditions

Relieves Dandruff

Gently Cleanses

LE SHAMPOOING

Conditionne

Supprime les Pellicules

Nettoie en Douceur

Keep out of reach of children

INDICATIONS AND USAGE

Better Braids Medicated Shampoo is a special no-lather formula for easy braids cleaning and maintenance. Salicylic acid aids in the control of dandruff flakes. Helps condition weak, damaged hair.

Use the Complete BETTER BRAIDS medicated product line daily for all your styling needs. Better Braids Spray relieves frizz, breakage and dandruff while adding sheen and moisture. Better Braids Leave-In Conditioner and Hair & Scalp Oil are a great finish for that perfect sheen. Better Braids Gel adds needed moisture to your scalp and hair. Better Braids Un-Braid is the perfect detangler.

Le Shampooing medicianl Better Braids contient une formule special pour le nettoyage et l'entretien des nattes. L'acide salicylique qu'il contient controle l'apparition des pellicules. Il aide a restaurer les cheveux abimes.

Utilisez au quotidien la ligne complete de produits medicinaux Better Braids pour tous les besoins de votre chevelure. La laque Better Braids controle la frisure, les pellicules tout et donnant un eclatant brillant et en hydratant le cheveu. Le conditionner Better Braids apporte la touche finale et donne un parfait eclat. Le Gel Better Braids hydrate a la fois la chevelure et le cuir chevelu. Le Demelant Better Braids est un produit parfait.

DOSAGE AND ADMINISTRATION

Directions: Spray this no-lather shampoo on dry or damp braids. Rinse with water and gently blot braids with towel to remove excess water. Can be used on all styles of hair.

Mode d'emploi: Vaporisez le shampooing sur les nattes seches ou humide. Rincez a l'eau et essuyez les nattes dans une serviette pour enlever l'exces d'eau. Peut etre utilise sur toutes sortes de cheveux.

warnings

INACTIVE INGREDIENT

Other Ingredients: aqua/water/eau, ammonium lauryl sulfate, propylene glycol, triethanolamine, hydromethyl benzene, propylene glycol, diaazolidinyl urea, methyl paraben, propyl paraben, sodium cocoamphoacetate, fragrance, disodium edta, vitamin e, aloe barbadensis, yellow #5, yellow #6

OTHER SAFETY INFORMATION

© 2010

PM BT 0425

MADE IN THE USA

Distributed by

KEYSTONE LABORATORIES

www.keystone-labs.com

Memphis, TN 38101-2026 USA

NW7 3SA London, United Kingdom